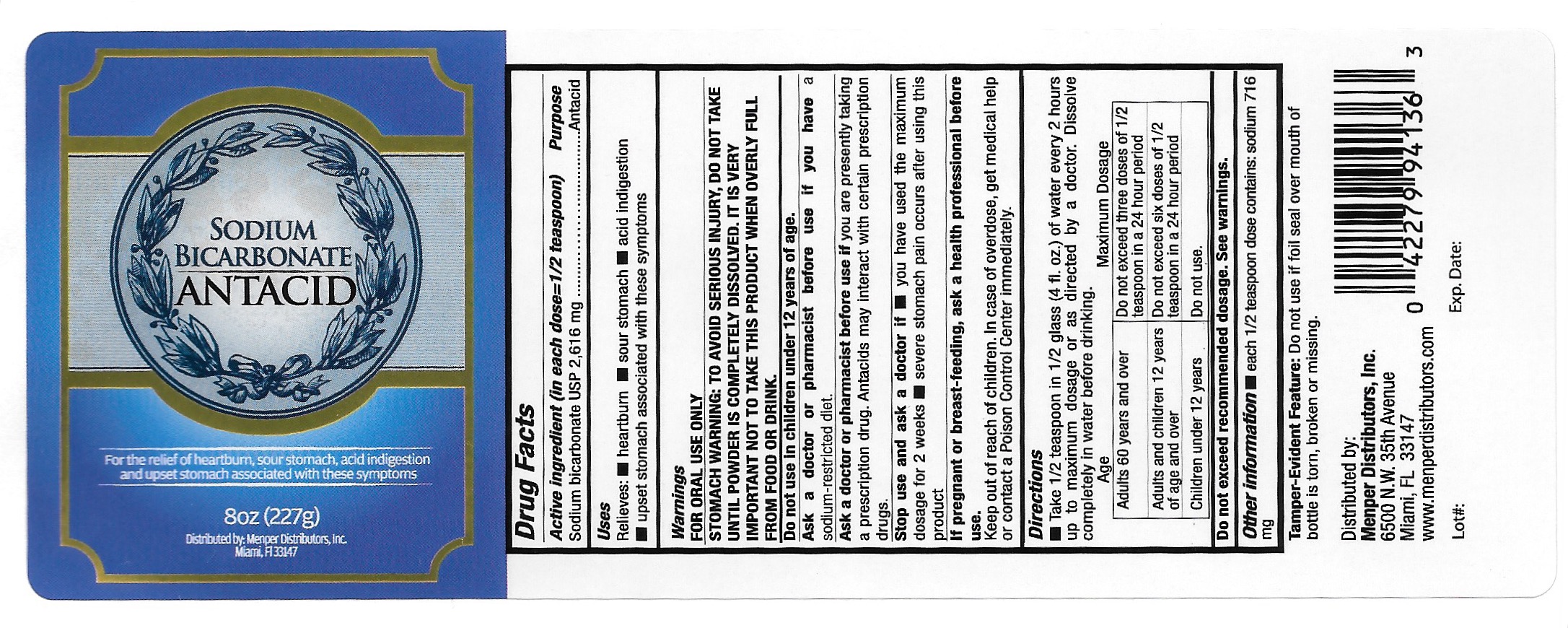 DRUG LABEL: Sodium Bicarbonate Antacid
NDC: 53145-390 | Form: POWDER
Manufacturer: Menper Distributors Inc.
Category: otc | Type: HUMAN OTC DRUG LABEL
Date: 20250722

ACTIVE INGREDIENTS: SODIUM BICARBONATE 2.616 g/2.616 g
INACTIVE INGREDIENTS: SODIUM CATION

Sodium Bicarbonate Antacid

Active ingredient (in each dose=1/2 teaspoon) Purpose

Sodium bicarbonate USP 2,616 mg ............................ Antacid

Purpose

Antacid

Uses

Relieves:

- heartburn
- sour stomach
- acid indigestion
- upset stomach associated with these syptoms

Warnings

FOR ORAL USE ONLY

STOMACH WARNING: TO AVOID SERIOUS INJURY, DO NOT TAKE UNTIL POWDER IS COMPLETELY DISSOLVED. IT IS VERY IMPORTANT NOT TO TAKE THIS PRODUCT WHEN OVERLY FILL FROM FOOD OR DRINK.

Do not use in children under 12 years of age.

Ask a doctor or pharmacist before use if you have a sodium-restricted diet.

Ask a doctor or pharmacist before use if you are presently taking a prescription drug. Antacids may interact with certain prescription drugs.

Stop use and ask a doctor if

- you have used the maximum dosage for 2 wekks
- sever stomach pain occurs after using this product

PREGNANCY OR BREAST FEEDING

If pregnant or breast-feeding, ask a health professional before use.

Keep out of reach of children. In case of overdose, get medical help or contact a Poison Control Center immediately.

Directions

- Take 1/2 teaspoon in 1/2 glass (4 fl. oz.) of water every 2 hours up to a maximum dosage or as directed by a doctor. Dissolve completely in water before drinking.

Age | Maximum Dosage
Adults 60 years and over | Do not exceed three doses of 1/2 teaspoon in a 24 hour period
Adults and children 12 years of age and over | Do not exceed six doses of 1/2 teaspoon in a 24 hour period
Children under 12 years | Do not use

Inactive Ingredients:

Questions:

1-800-560-5223 M-F 9AM to 4PM Eastern

Menper Distributors Inc.

www.menperdistributors.com